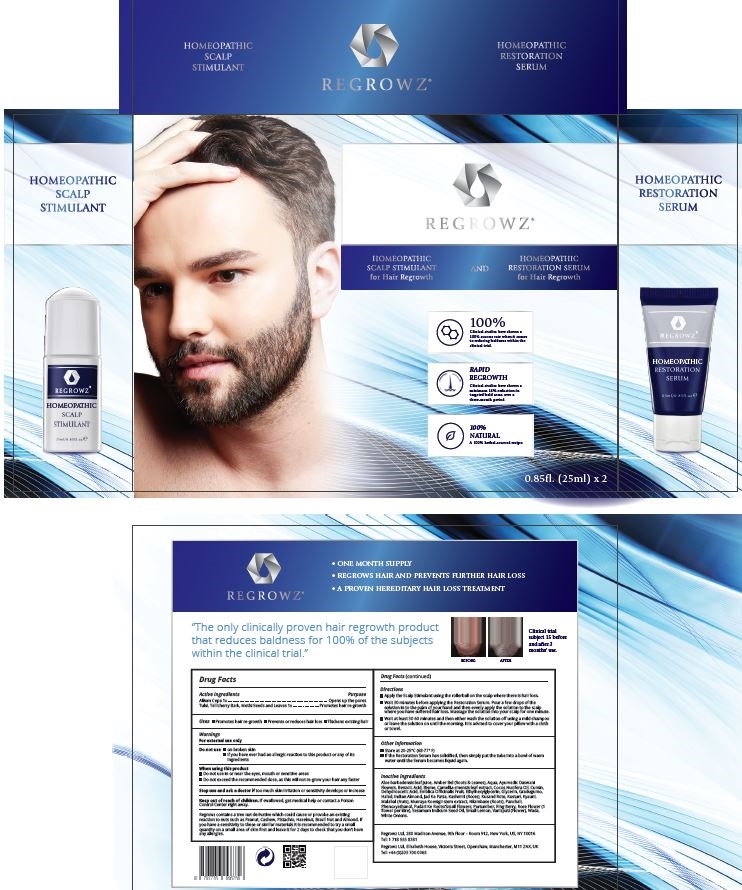 DRUG LABEL: Regrowz Homeopathic Scalp Stimulant
NDC: 70878-001 | Form: SYRUP
Manufacturer: Regrowz Ltd
Category: homeopathic | Type: HUMAN OTC DRUG LABEL
Date: 20180627

ACTIVE INGREDIENTS: ALLIUM CEPA WHOLE 0.1 [hp_X]/25 mg; FENUGREEK LEAF 0.1 [hp_X]/25 mg; HOLY BASIL LEAF 0.1 [hp_X]/25 mg; HOLARRHENA PUBESCENS BARK 0.1 [hp_X]/25 mg
INACTIVE INGREDIENTS: CULLEN CORYLIFOLIUM SEED; GARLIC; GINGER; MELALEUCA ALTERNIFOLIA WHOLE; MYRISTICA FRAGRANS WHOLE; CAMELLIA SINENSIS SEED OIL; LEMON; OCIMUM TENUIFLORUM TOP; CUMIN; WATER; ALOE VERA LEAF; ACORUS CALAMUS ROOT; GREEN PEPPERCORN; LAVANDULA ANGUSTIFOLIA SUBSP. ANGUSTIFOLIA WHOLE

Regrowz Stimulant

Purpose
Opens up the pores Promotes hair re-growth

Active Ingredients

Allium Cepa 1x
Tulsi, Tellicherry Bark, Methi Seeds and Leaves 1x

Uses

Promotes hair re-growth Prevents or reduces hair loss Thickens existing hair

Warnings -
For external use only
Do not use on broken skin
if you have ever had an allergic reaction to this product or any of its ingredients

Stop use and ask a doctor if too much skin irritation or sensitivity develops or increase

When using this product
Do not use in or near the eyes, mouth or sensitive areas
Do not exceed the recommended dose, as this will not re-grow your hair any faster

Directions

- Apply the Scalp Stimulant using the rollerball on the scalp where there is hair loss.

- Wait 30 minutes before applying the Restoration Serum. Pour a few drops of the solution in to the palm of your hand and then evenly apply the solution to the scalp where you have suﬀered hair loss. Massage the solution into your scalp for one minute.

- Wait at least 30-60 minutes and then either wash the solution oﬀ using a mild shampoo or leave the solution on until the morning.

It is advised to cover your pillow with a cloth or towel.

Keep out of reach of children.

If swallowed, get medical help or contact a Poison Control Center right away.

Inactive ingredients

Aloe barbadensis leaf juice, Amber Bel (Roots & Leaves), Aqua, Ayurvedic Daswani Flowers, Benzoic Acid, Bisme, Camellia sinensis leaf extract, Cocos Nucifera Oil, Cumin, Dehydroacetic Acid, Emblica Oﬃcinalis Fruit, Ethylhexylglycerin, Glycerin, Gradugumo, Halad, Indian Almond, Jad Ka Patta, Kashmiri (Roots), Kusand Rote, Kusturi, Kyauni, Malabal (Nuts), Murraya Koenigii stem extract, Nilambase (Roots), Panchali, Phenoxyethanol, Pudari Ke Roots/Small Flowers, Purtumber, Ring Berry, Rose Flower (1 ﬂower per litre), Sesamum Indicum Seed Oil, Small Lemon, Vanispati (Flower), Wada, White Onions.

Other information

Store at 20-25ºC (68-77ºF)
If the Restoration Serum has solidiﬁed, then simply put the tube into a bowl of warm water until the Serum becomes liquid again.